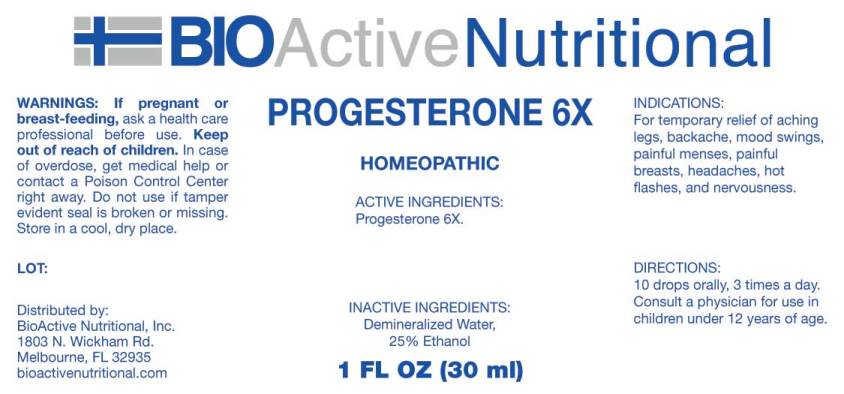 DRUG LABEL: Progesterone
NDC: 43857-0120 | Form: LIQUID
Manufacturer: BioActive Nutritional, Inc.
Category: homeopathic | Type: HUMAN OTC DRUG LABEL
Date: 20180502

ACTIVE INGREDIENTS: PROGESTERONE 6 [hp_X]/1 mL
INACTIVE INGREDIENTS: WATER; ALCOHOL

Drug Facts:

ACTIVE INGREDIENTS:

Progesterone 6X.

INDICATIONS:

For temporary relief of aching legs, backache, mood swings, painful menses, painful breasts, headaches, hot flashes, and nervousness.

WARNINGS:

If pregnant or breast-feeding, ask a health professional before use.

Keep out of reach of children. In case of overdose, get medical help or contact a Poison Control Center right away.

Do not use if tamper evident seal is broken or missing.

Store in cool, dry place.

DIRECTIONS:

10 drops orally, 3 times a day. Consult a physician for use in children under 12 years of age.

INACTIVE INGREDIENTS:

Demineralized Water, 25% Ethanol.

KEEP OUT OF REACH OF CHILDREN. In case of overdose, get medical help or contact a Poison Control Center right away.

INDICATIONS:

For temporary relief of aching legs, backache, mood swings, painful menses, painful breasts, headaches, hot flashes, and nervousness.

QUESTIONS:

Distributed by:

BioActive Nutritional, Inc.

1803 N. Wickham Rd.

Melbourne, FL 32935

bioactivenutritional.com

PACKAGE LABEL DISPLAY:

BIOActive Nutritional
PROGESTERONE 6X
HOMEOPATHIC
1 FL OZ (30 ml)